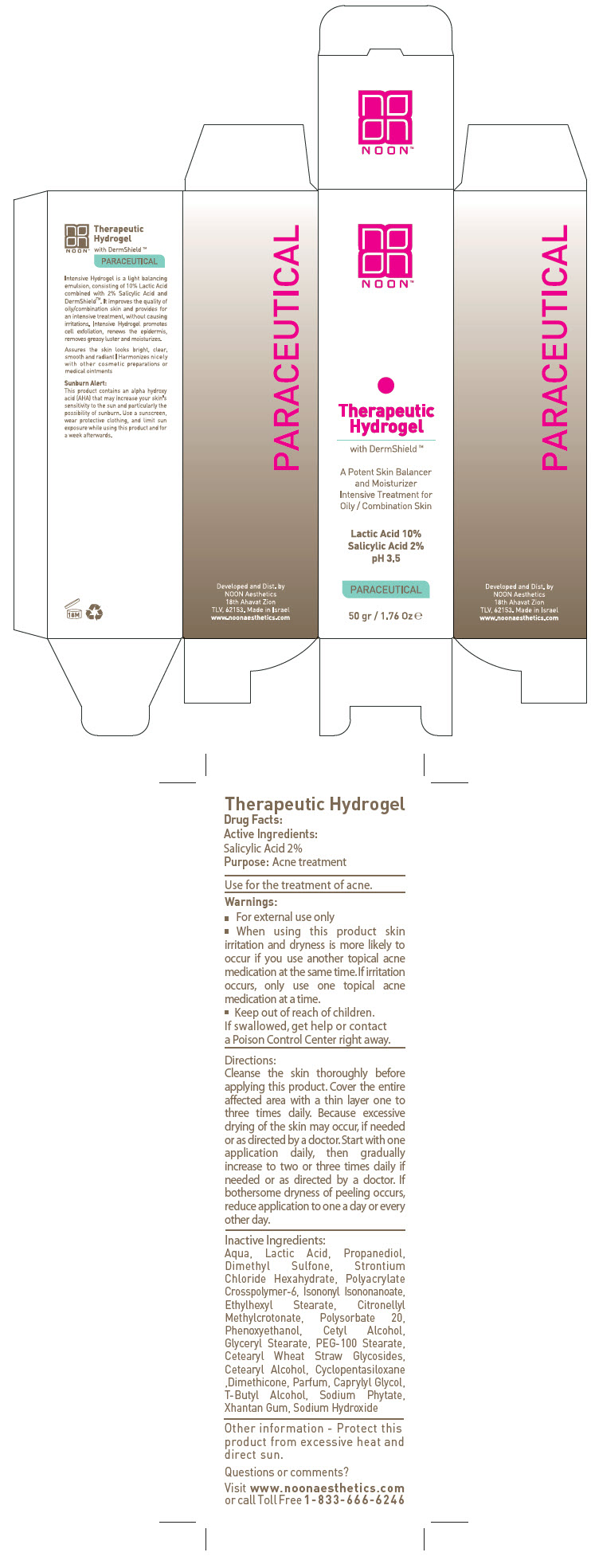 DRUG LABEL: Therapeutic Hydrogel
NDC: 78863-1090 | Form: CREAM
Manufacturer: Noon Aesthetics M.R. Ltd
Category: otc | Type: HUMAN OTC DRUG LABEL
Date: 20260115

ACTIVE INGREDIENTS: Salicylic Acid 1 g/50 g
INACTIVE INGREDIENTS: Polysorbate 20; Propanediol; Water; Phytate Sodium; Dimethyl Sulfone; Strontium Chloride Hexahydrate; Xanthan Gum; Ammonium Acryloyldimethyltaurate, Dimethylacrylamide, Lauryl Methacrylate And Laureth-4 Methacrylate Copolymer, Trimethylolpropane Triacrylate Crosslinked (45000 Mpa.S); Tert-Butyl Alcohol; LACTIC ACID, DL-; Sodium Hydroxide; Cetearyl Wheat Straw Glycosides; Cetostearyl Alcohol; Isononyl Isononanoate; OCTYL STEARATE; Cetyl Alcohol; Glyceryl Monostearate; PEG-100 MONOSTEARATE; Phenoxyethanol; Caprylyl Glycol; Citronellyl Methylcrotonate; Cyclomethicone 5; DIMETHICONE, UNSPECIFIED

Therapeutic Hydrogel

Drug Facts:

Active Ingredients

Salicylic Acid 2%

Purpose

Acne treatment

INDICATIONS AND USAGE

Use for the treatment of acne.

Warnings

- For external use only

- When using this product skin irritation and dryness is more likely to occur if you use another topical acne medication at the same time. If irritation occurs, only use one topical acne medication at a time.

- Keep out of reach of children.

If swallowed, get help or contact a Poison Control Center right away.

Directions

Cleanse the skin thoroughly before applying this product. Cover the entire affected area with a thin layer one to three times daily. Because excessive drying of the skin may occur, if needed or as directed by a doctor. Start with one application daily, then gradually increase to two or three times daily if needed or as directed by a doctor. If bothersome dryness of peeling occurs, reduce application to one a day or every other day.

Inactive Ingredients

Aqua, Lactic Acid, Propanediol, Dimethyl Sulfone, Strontium Chloride Hexahydrate, Polyacrylate Crosspolymer-6, Isononyl Isononanoate, Ethylhexyl Stearate, Citronellyl Methylcrotonate, Polysorbate 20, Phenoxyethanol, Cetyl Alcohol, Glyceryl Stearate, PEG-100 Stearate, Cetearyl Wheat Straw Glycosides, Cetearyl Alcohol, Cyclopentasiloxane ,Dimethicone, Parfum, Caprylyl Glycol, T-Butyl Alcohol, Sodium Phytate, Xhantan Gum, Sodium Hydroxide

Other information

Protect this product from excessive heat and direct sun.

Questions or comments?

Visit www. noonaesthetics.com or call Toll Free 1-833-666-6246

Developed and Dist. by
NOON Aesthetics
18th Ahavat Zion
TLV, 62153.

PRINCIPAL DISPLAY PANEL - 50 gr Bottle Carton

NOON™

Therapeutic
Hydrogel
with DermShield™

A Potent Skin Balancer
and Moisturizer
Intensive Treatment for
Oily / Combination Skin

Lactic Acid 10%
Salicyclic Acid 2 %
pH 3.5

PARACEUTICAL

50 gr / 1.76 Oz ℮